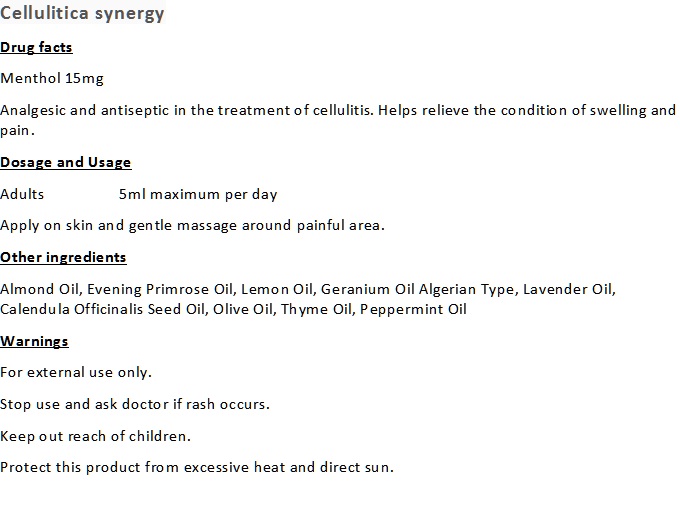 DRUG LABEL: Cellulitica Synergy
NDC: 70470-1006 | Form: OIL
Manufacturer: PHYTOPIA CO., LTD.
Category: otc | Type: HUMAN OTC DRUG LABEL
Date: 20191231

ACTIVE INGREDIENTS: MENTHOL 1.5 g/50 g
INACTIVE INGREDIENTS: THYME OIL; PEPPERMINT OIL; CALENDULA OFFICINALIS SEED OIL; ALMOND OIL; PHENOL; OLIVE OIL; LEMON OIL; GERANIUM OIL, ALGERIAN TYPE; LAVENDER OIL; EVENING PRIMROSE OIL

active ingredient

menthol(1%) analgesic, External
Uses

Uses

Helps relieve the condition of cellulitis infection.

Dosage Suggestion

Adults 10ml maximum per day,

Directions

Apply on skin and gentle massage around infected area.

Inactive Ingredient

Thyme Oil, Peppermint Oil, Lemon Oil, Lavender Oil, Geranium Oil (Algerian Type), Olive Oil, Almond Oil, Sunflower Oil, Evening Primrose Oil, Calendula Officinalis Seed Oil.

Warning

- For external use only.
- Stop use and ask doctor if rash occurs.
- Keep out reach of children.

Warning

Keep out reach of children.

Other Information

Protect this product from excessive heat and direct sun.